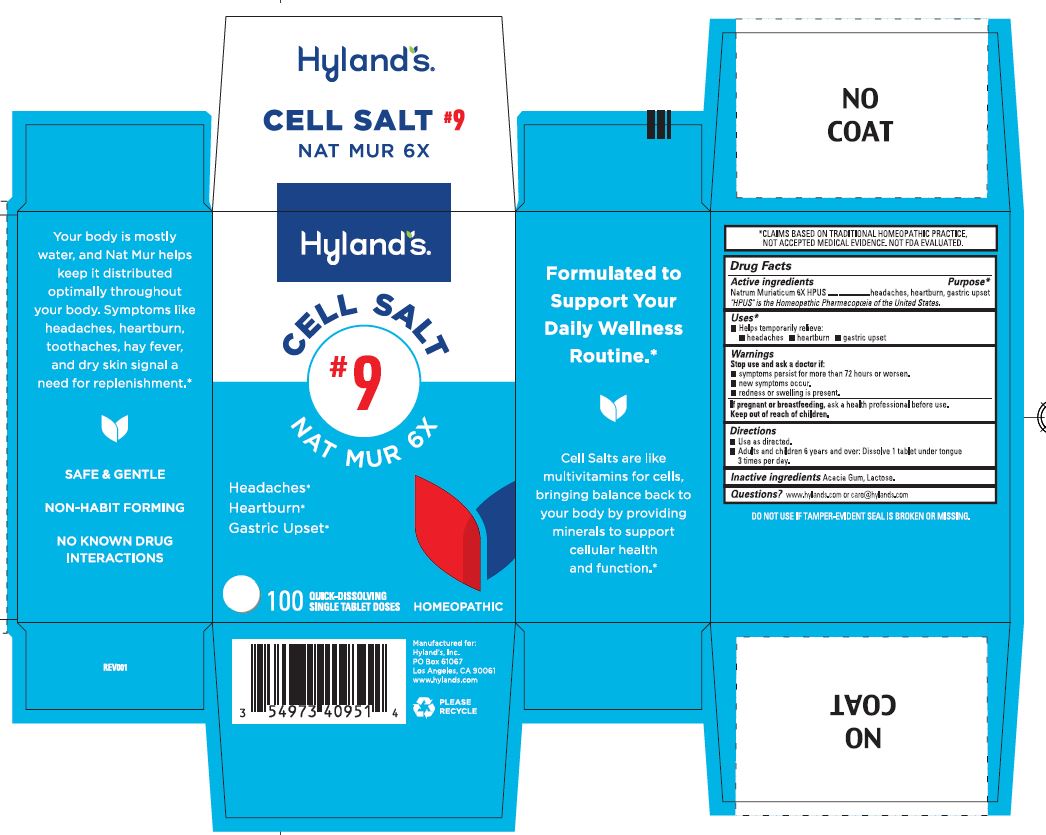 DRUG LABEL: Nat Mur 6X
NDC: 54973-4095 | Form: TABLET, SOLUBLE
Manufacturer: Hyland's Inc.
Category: homeopathic | Type: HUMAN OTC DRUG LABEL
Date: 20250410

ACTIVE INGREDIENTS: SODIUM CHLORIDE 6 [hp_X]/1 1
INACTIVE INGREDIENTS: ACACIA; LACTOSE MONOHYDRATE

Cell Salt #9 Nat Mur 6X

Drug Facts

Active ingredients | Purpose
Natrum Muriaticum 6X HPUS | headaches, heartburn, gastric upset

"HPUS" is the Homeopathic Pharmacopoeia of the United States.

Uses

■ Temporarily relieves:
■ headaches ■ heartburn ■ gastric upset

Warnings

Stop use and ask a doctor if

■ symptoms persist for more than 72 hours or worsen.
■ new symptoms occur.
■ redness or swelling is present.

If pregnant or breastfeeding

Ask a health professional before use.

Directions

■ Use as directed.
■ Adults and children 6 years and over: Dissolve 1 tablet under tongue 3 times per day.

Inactive ingredients

Acacia Gum, Lactose.

Questions?

www.hylands.com or care@hylands.com

PURPOSE

Headaches

Heartburn

Gastric Upset

PRINCIPAL DISPLAY PANEL

Hyland's

CELL SALT

#9

NAT MUR 6X

Headaches*

Heartburn*

Gastric Upset*

100

QUICK-DISSOLVING

SINGLE TABLET DOSES

HOMEOPATHIC